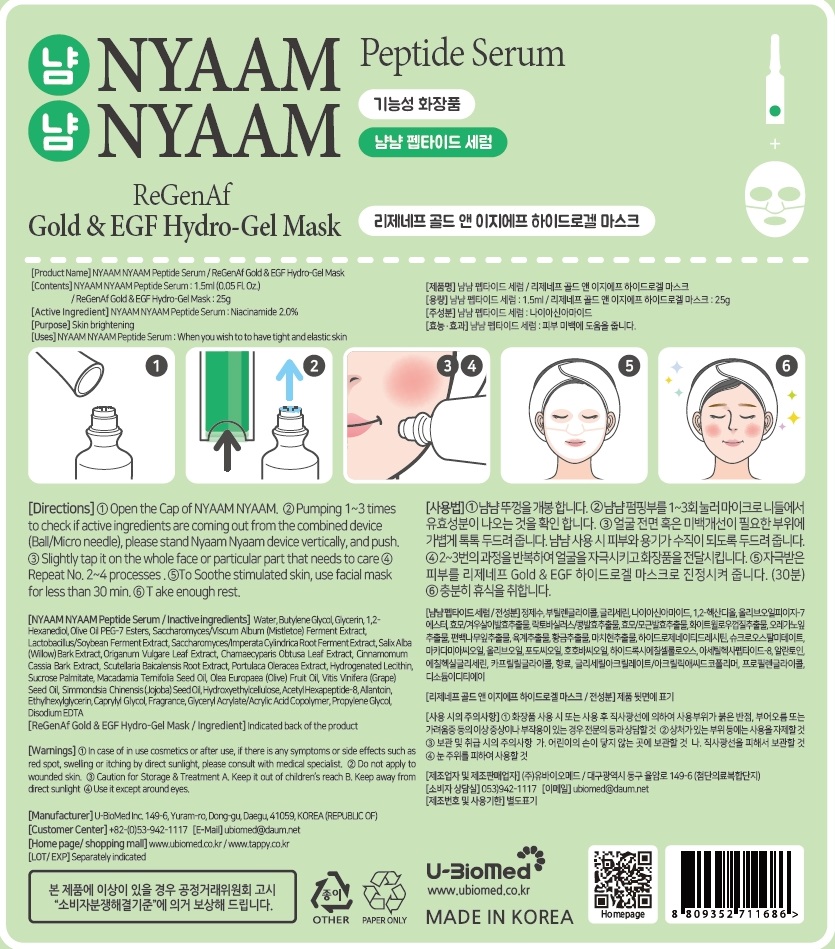 DRUG LABEL: NYAAM NYAAM Peptide Serum
NDC: 72108-040 | Form: LIQUID
Manufacturer: U-BioMed Inc.
Category: otc | Type: HUMAN OTC DRUG LABEL
Date: 20180308

ACTIVE INGREDIENTS: Niacinamide 0.03 g/1.5 mL
INACTIVE INGREDIENTS: Water; Butylene Glycol

ACTIVE INGREDIENT

Active ingredients: Niacinamide 2.0%

INACTIVE INGREDIENT

Inactive ingredients:

Water, Butylene Glycol, Glycerin, 1,2-Hexanediol, Olive Oil PEG-7 Esters, Saccharomyces/Viscum Album (Mistletoe) Ferment Extract, Lactobacillus/Soybean Ferment Extract, Saccharomyces/Imperata Cylindrica Root Ferment Extract, Salix Alba (Willow) Bark Extract, Origanum Vulgare Leaf Extract, Chamaecyparis Obtusa Leaf Extract, Cinnamomum Cassia Bark Extract, Scutellaria Baicalensis Root Extract, Portulaca Oleracea Extract, Hydrogenated Lecithin, Sucrose Palmitate, Macadamia Ternifolia Seed Oil, Olea Europaea (Olive) Fruit Oil, Vitis Vinifera (Grape) Seed Oil, Simmondsia Chinensis (Jojoba) Seed Oil, Hydroxyethylcellulose, Acetyl Hexapeptide-8, Allantoin, Ethylhexylglycerin, Caprylyl Glycol, Fragrance, Glyceryl Acrylate/Acrylic Acid Copolymer, Propylene Glycol, Disodium EDTA

PURPOSE

Purpose: Skin brightening

WARNINGS

1. In case of in use cosmetics or after use, if there is any symptoms or side effects such as red spot, swelling or itching by direct sunlight, please consult with medical specialist.

2. Do not apply to wounded skin.

3. Caution for Storage & Treatment A. Keep it out of children’s reach B. Keep away from direct sunlight

4. Use it except around eyes.

KEEP OUT OF REACH OF CHILDREN

Keep it out of children’s reach

Uses

When you wish to to have tight and elastic skin.

Directions

1. Open the cap of Nyaam Nyaam.

2. Pumping 1~3 times to check if activate ingredients are coming out from the combined device (Ball/ Micro needle) – Serum is put into airless container so to come out its solution through the combined device(Ball/ Micro needle), please stand Nyaam Nyaam device vertically, and push.

3. Slightly tap it on the whole face or particular that needs to care.

4. Repeat No. 2~4 processes.

5. To soothe stimulated skin, use facial mask for less than 30min.

6. Take enough rest.

QUESTIONS

E-Mail : ubiomed@daum.net

Home page / Shopping mall : www.ubiomed.co.kr / www.tappy.co.kr

Call : +82 53 942 1117